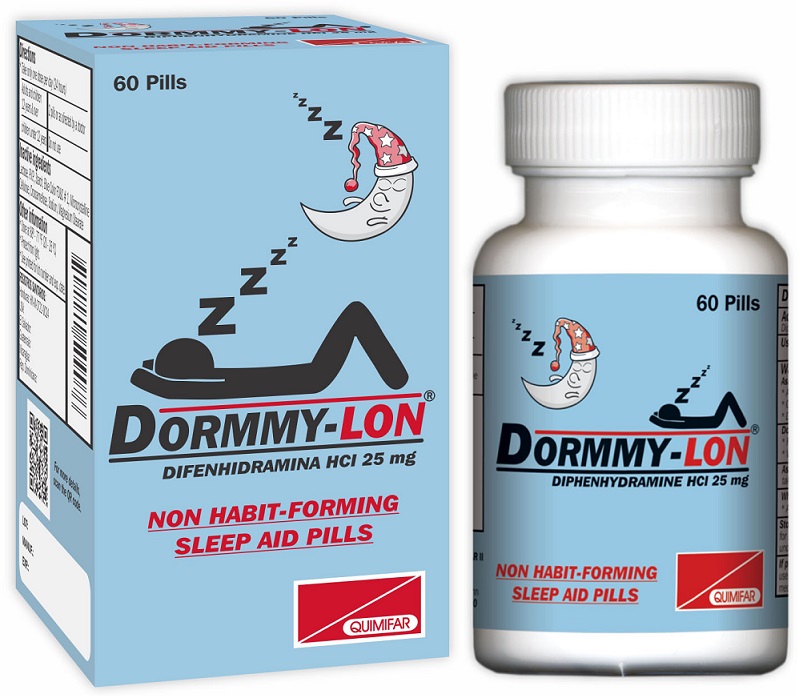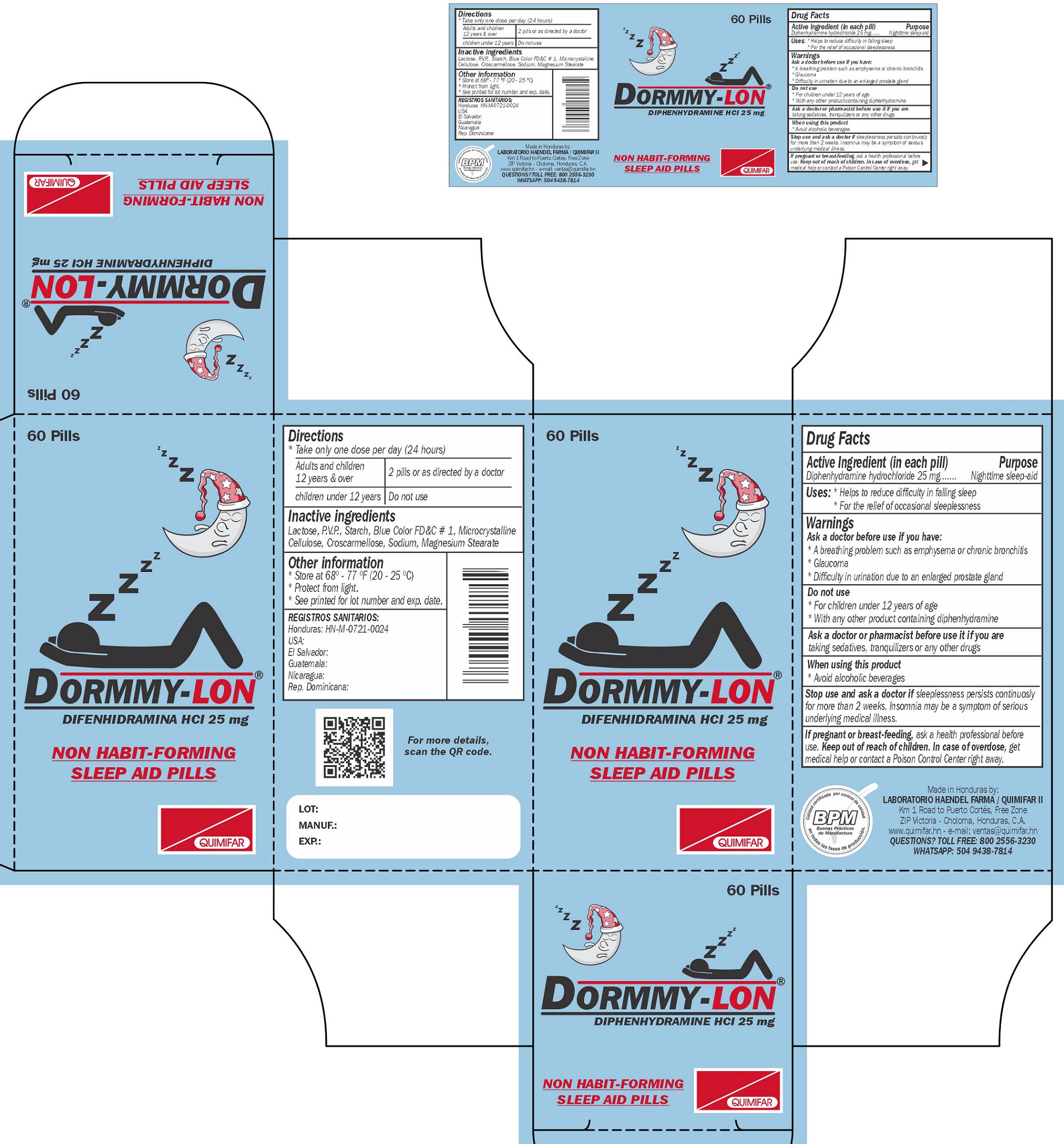 DRUG LABEL: DORMMY-LON
NDC: 83164-000 | Form: TABLET
Manufacturer: Haendel Farma, S.A. de C.V.
Category: otc | Type: HUMAN OTC DRUG LABEL
Date: 20260127

ACTIVE INGREDIENTS: DIPHENHYDRAMINE HYDROCHLORIDE 25 mg/1 1
INACTIVE INGREDIENTS: SODIUM; MAGNESIUM STEARATE; LACTOSE, UNSPECIFIED FORM; POVIDONE, UNSPECIFIED; FD&C BLUE NO. 1; MICROCRYSTALLINE CELLULOSE; CROSCARMELLOSE

DORMMY-LON

Active Ingredient (in each pill)

Diphenhydramine hydrochloride 25 mg

Purpose

Nighttime sleep-aid

Uses:

- Helps to reduce difficulty in falling sleep
- For the relief of occasional sleeplessness

Warnings

Ask a doctor before use if you have:

- A breathing problem such as emphysema or chronic bronchitis
- Glaucoma
- Difficulty in urination due to an enlarged prostate gland

Do not use

- For children under 12 years of age
- With any other product containing diphehydramine

Ask a doctor or pharmacist before use it if you are

taking sedatives, tranquilizers or any other drugs

When using this product

- Avoid alcoholic beverages

Stop use and ask a doctor if

sleeplessness persists continuosly for more than 2 weeks, In sommia may be a symptom of serious underlying medical illness.

If pregnant or breast-feeding,

ask a health professional before use.

Keep out of reach of children.

In case of overdose, get medical help or contact a Poison Control Center right away.

Directions

- Take only one dose per day (24 hours)

Adults and children 12 years & over | 2 pills or as directed by a doctor
children under 12 years | Do not use

Inactive ingredients

Lactose, P.V.P., Starch, Blue Color FD&C # 1, Microcrystalline Cellulose, Croscarmellose, Sodium, Magnesium Stearate

Other information

- Store at 68° - 77 °F (20-25 °C)
- Protect from light.
- See printed for lot number and exp. date.